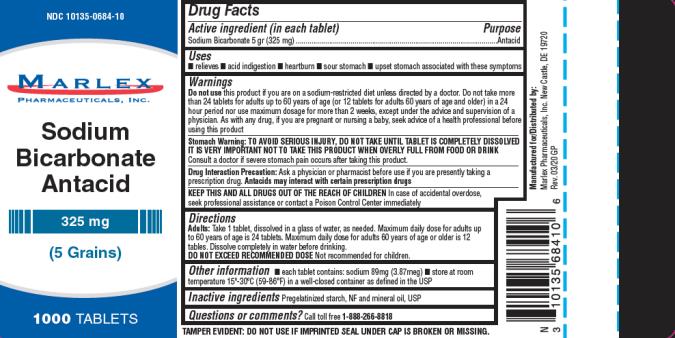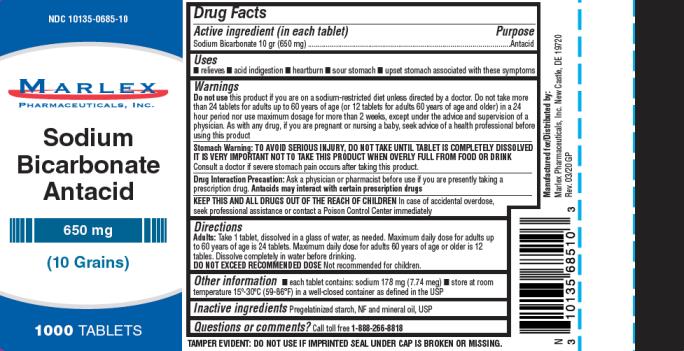 DRUG LABEL: Sodium Bicarbonate
NDC: 10135-684 | Form: TABLET
Manufacturer: Marlex Pharmaceuticals Inc
Category: otc | Type: HUMAN OTC DRUG LABEL
Date: 20200520

ACTIVE INGREDIENTS: SODIUM BICARBONATE 325 mg/1 1
INACTIVE INGREDIENTS: STARCH, CORN; MINERAL OIL

Sodium Bicarbonate Tablets

SODIUM BICARBONATE - sodium bicarbonate tablet

Marlex Pharmaceuticals, Inc.

Disclaimer: Most OTC drugs are not reviewed and approved by FDA; however, they may be marketed if they comply with applicable regulations and policies. FDA has not evaluated whether this product complies.

----------

Sodium Bicarbonate

Active ingredient (in each tablet)

Sodium bicarbonate 10 gr (650 mg)

Sodium bicarbonate 5gr (325 mg)

Purpose

Antacid

Uses

Relieves

- acid indigestion heartburn
- sour stomach
- upset stomach associated with these symptoms

Warnings

Ask a doctor before use if you have

a sodium restricted diet

Ask a doctor or pharmacist before use if you are

taking a prescription drug. Antacids may interact with certain prescription drugs.

Stop use and ask a doctor if

symptoms last more than 2 weeks

If pregnant or breast-feeding,

ask a health professional before use.

Directions

- do not use the maximum dosage for more than 2 weeks
- dissolve tablets completely in water prior to use

325mg,

- adults 60 years of age and over: 2-8 tablets every 4 hours, not more than 24 tablets in 24 hours
- adults under 60 years of age: 2-8 tablets every 4 hours, not more than 48 tablets in 24 hours

650mg,

- adults 60 years of age and over: 1-2 tablets every 4 hours, not more than 12 tablets in 24 hours
- adults under 60 years of age: 1-4 tablets every 4 hours, not more than 24 tablets in 24 hours

Other information

- each tablet contains: sodium 89mg (325mg)
- store at room temperature 15°-30°C (59°-86°F) in well-closed containers as defined in the USP

sodium 178 mg (650mg)

Inactive ingredients

Pregelatinized starch, NF and mineral oil, USP

Questions or comments?

Call toll free 1-888-266-8818

TAMPER EVIDENT: DO NOT USE IF IMPRINTED SAFETY SEAL UNDER CAP IS BROKEN OR MISSING

PRINCIPAL DISPLAY PANEL

NDC 10135-684-10

Marlex Pharmaceuticals, Inc.

Sodium Bicarbonate

Sodium Bicarbonate 5 gr (325 mg) Antacid

1000 Tablets

PRINCIPAL DISPLAY PANEL

NDC 10135-685-10

Marlex Pharmaceuticals, Inc.

Sodium Bicarbonate

Sodium Bicarbonate 10gr (650 mg) Antacid

1000 Tablets